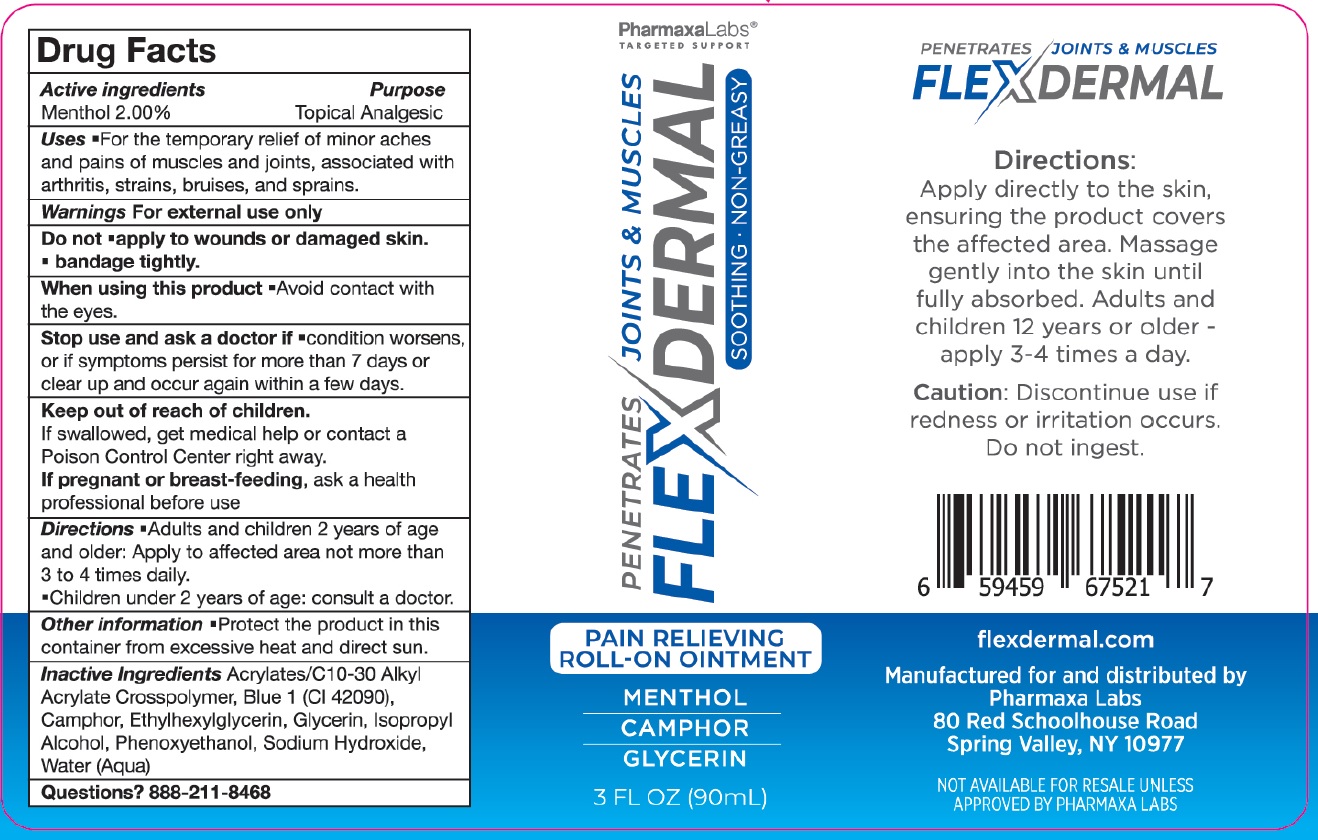 DRUG LABEL: FlexDermal Pain Relieving Roll-On
NDC: 84197-867 | Form: LIQUID
Manufacturer: SOLVADERM LLC
Category: otc | Type: HUMAN OTC DRUG LABEL
Date: 20250206

ACTIVE INGREDIENTS: MENTHOL 20 mg/1 mL
INACTIVE INGREDIENTS: FD&C BLUE NO. 1; ETHYLHEXYLGLYCERIN; GLYCERIN; ISOPROPYL ALCOHOL; PHENOXYETHANOL; SODIUM HYDROXIDE; WATER

FlexDermal Pain Relieving Roll-On Ointment

Active ingredients

Menthol 2.00%

Purpose

Topical Analgesic

Uses

- For the temporary relief of minor aches and pains of muscles and joints, associated with arthritis, strains, bruises, and sprains.

Warnings

For external use only

Do not

- apply to wounds or damaged skin.
- bandage tightly.

When using this product

- Avoid contact with the eyes.

Stop use and ask a doctor if

- condition worsens, or if symptoms persist for more than 7 days or clear up and occur again within a few days.

Keep out of reach of children.

If swallowed, get medical help or contact a Poison Control Center right away.

If pregnant or breast-feeding,

ask a health professional before use

Directions

- Adults and children 2 years of age and older: Apply to affected area not more than 3 to 4 times daily.
- Children under 2 years of age: consult a doctor.

Other information

- Protect the product in this container from excessive heat and direct sun.

Inactive Ingredients

Acrylates/C10-30 Alkyl Acrylate Crosspolymer, Blue 1 (CI 42090), Camphor, Ethylhexylglycerin, Glycerin, Isopropyl Alcohol, Phenoxyethanol, Sodium Hydroxide, Water(Aqua)

Questions?

888-211-8468